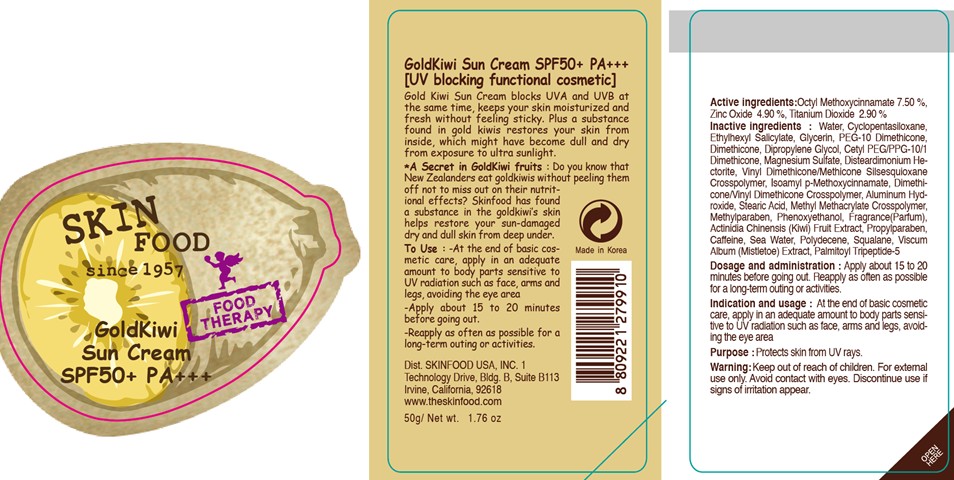 DRUG LABEL: GOLDKIWI SUN
NDC: 76214-013 | Form: CREAM
Manufacturer: SKINFOOD CO., LTD.
Category: otc | Type: HUMAN OTC DRUG LABEL
Date: 20110907

ACTIVE INGREDIENTS: OCTINOXATE 3.75 g/50 g; ZINC OXIDE 2.45 g/50 g; TITANIUM DIOXIDE 1.45 g/50 g
INACTIVE INGREDIENTS: WATER; CYCLOMETHICONE 5; GLYCERIN; DIMETHICONE; ALUMINUM HYDROXIDE; STEARIC ACID; METHYLPARABEN; PHENOXYETHANOL; KIWI FRUIT; PROPYLPARABEN; CAFFEINE; SQUALANE; PALMITOYL TRIPEPTIDE-5

Drug Facts

ACTIVE INGREDIENT

Active ingredients: OCTINOXATE 7.5%, ZINC OXIDE 4.90%, TITANIUM DIOXIDE 2.90%

Inactive ingredients:
Water, Cyclopentasiloxane, Ethylhexyl Salicylate, Glycerin, PEG-10 Dimethicone, Dimethicone, Dipropylene Glycol, Cetyl PEG/PPG-10/1 Dimethicone, Magnesium Sulfate, Disteardimonium Hectorite, Vinyl Dimethicone/Methicone Silsesquioxane Crosspolymer, Isoamyl p-Methoxycinnamate, Dimethicone/Vinyl Dimethicone Crosspolymer, Aluminum Hydroxide, Stearic Acid, Methyl Methacrylate Crosspolymer, Methylparaben, Phenoxyethanol, Fragrance(Parfum), Actinidia Chinensis (Kiwi) Fruit Extract, Propylparaben, Caffeine, Sea Water, Polydecene, Squalane, Viscum Album (Mistletoe) Extract, Palmitoyl Tripeptide-5

Purpose: Protects skin from UV rays.

Warnings:
For external use only. Avoid contact with eyes.
Discontinue use if signs of irritation appear.

Keep out of reach of children:
Keep out of reach of children.

Indication and usage:
At the end of basic cosmetic care, apply in an adequate amount to body parts sensitive to UV radiation such as face, arms and legs, avoiding the eye area.

Dosage and administration:
Apply about 15 to 20 minutes before going out.
Reapply as often as possible for a long-term outing or activities.